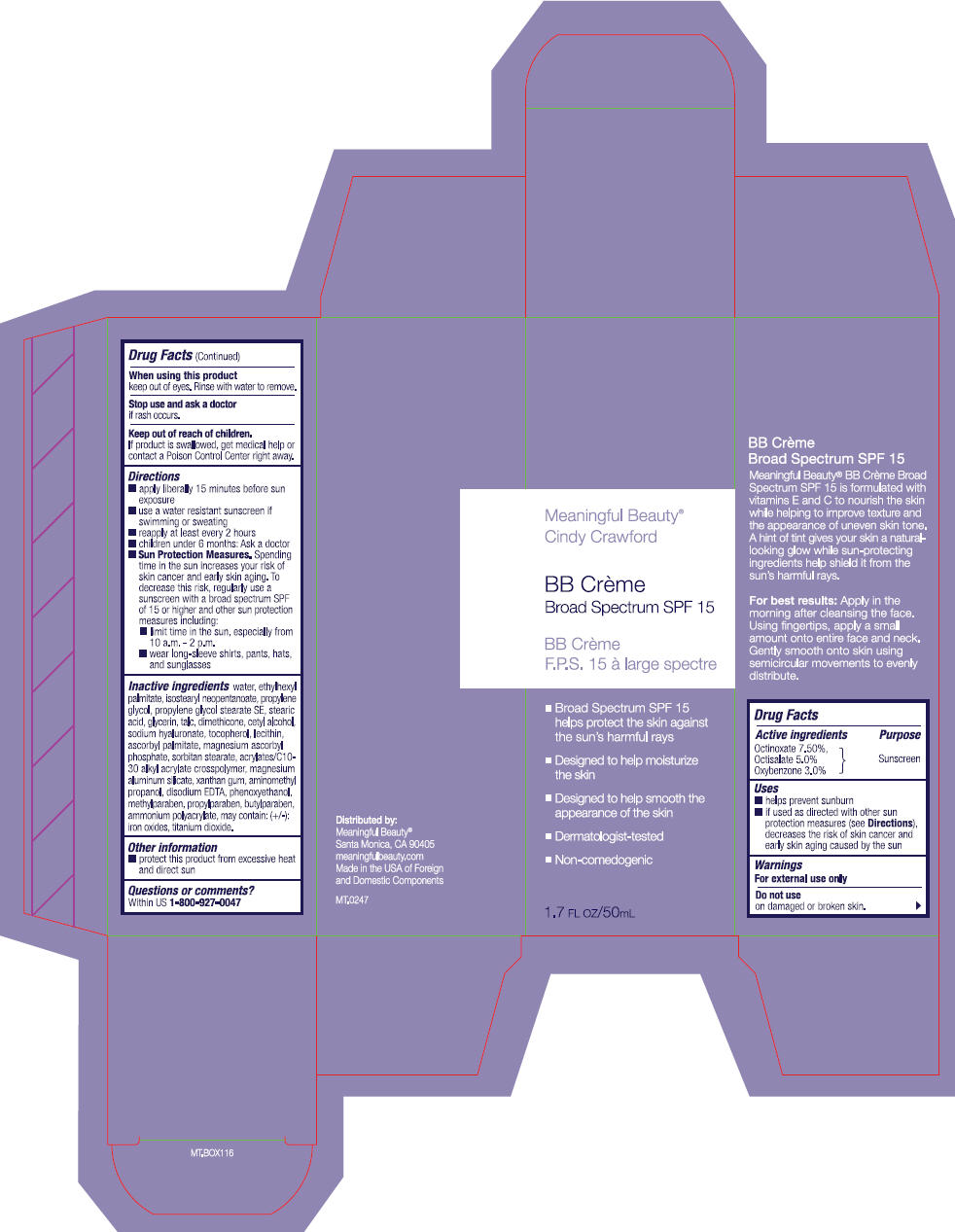 DRUG LABEL: Meaningful Beauty BB Broad Spectrum SPF 15 (Light, Medium, Dark)
NDC: 70605-008 | Form: LOTION
Manufacturer: Guthy-Renker LLC
Category: otc | Type: HUMAN OTC DRUG LABEL
Date: 20161004

ACTIVE INGREDIENTS: OCTINOXATE 7.5 mg/100 mL; OCTISALATE 5 mg/100 mL; OXYBENZONE 3 mg/100 mL
INACTIVE INGREDIENTS: WATER; ETHYLHEXYL PALMITATE; PROPYLENE GLYCOL; STEARIC ACID; GLYCERIN; TALC; DIMETHICONE; .ALPHA.-TOCOPHEROL; ASCORBYL PALMITATE; HYALURONATE SODIUM; LECITHIN, SOYBEAN; XANTHAN GUM; CETYL ALCOHOL; SORBITAN MONOSTEARATE; MAGNESIUM ALUMINUM SILICATE; CARBOMER INTERPOLYMER TYPE A (ALLYL SUCROSE CROSSLINKED); MAGNESIUM ASCORBYL PHOSPHATE; TROLAMINE; EDETATE DISODIUM; ISOSTEARYL NEOPENTANOATE; PROPYLENE GLYCOL MONOPALMITOSTEARATE; PHENOXYETHANOL; METHYLPARABEN; PROPYLPARABEN; BUTYLPARABEN; METHYLISOTHIAZOLINONE; FERRIC OXIDE RED; FERRIC OXIDE YELLOW; FERROSOFERRIC OXIDE; TITANIUM DIOXIDE

Meaningful Beauty® BB Cream Broad Spectrum SPF 15 (Light, Medium, Dark)

Drug Facts

Active ingredients

Octinoxate 7.5%
Octisalate 5.0%
Oxybenzone 3.0%

Purpose

Sunscreen

Uses

- helps prevent sunburn
- if used as directed with other sun protection measures (see Directions), decreases the risk of skin cancer and early skin aging caused by the sun

Warnings

For external use only

Do not use

on damaged or broken skin.

When using this product

keep out of eyes. Rinse with water to remove.

Stop use and ask a doctor

if rash occurs.

Keep out of reach of children.

If product is swallowed, get medical help or contact a Poison Control Center right away.

Directions

- apply liberally 15 minutes before sun exposure
- reapply:
  - after 40 minutes of swimming or sweating
  - immediately after towel drying
  - at least every 2 hours
- Sun Protection Measures.
  Spending time in the sun increases your risk of skin cancer and early skin aging. To decrease this risk, regularly use a sunscreen with a broad spectrum SPF of 15 or higher and other sun protection measures including:
  - limit time in the sun, especially from 10 a.m. - 2 p.m.
  - wear long-sleeve shirts, pants, hats, and sunglasses
- children under 6 months: Ask a doctor

Inactive ingredients

water, ethylhexyl palmitate, isostearyl neopentanoate, propylene glycol, stearic acid, propylene glycol stearate SE, glycerin, talc, dimethicone, cetyl alcohol, magnesium ascorbyl phosphate, tocopherol, ascorbyl palmitate, sodium hyaluronate, lecithin, xanthan gum, sorbitan stearate, magnesium aluminum silicate, acrylates/C10-30 alkyl acrylate crosspolymer, ammonium polyacrylate, triethanolamine, disodium EDTA, phenoxyethanol, methylparaben, propylparaben, butylparaben, methylisothiazolinone. may contain (+/-) : iron oxides (CI 77491, CI 77492, CI 77499), titanium dioxide (CI 77891)

Other information

- protect this product from excessive heat and direct sun

Questions or comments?

Within US 1-800-950-4465

Distributed by:
Meaningful Beauty®
Santa Monica, CA 90405

PRINCIPAL DISPLAY PANEL - 50 mL Tube Box

Meaningful Beauty®
Cindy Crawford

BB Crème
Broad Spectrum SPF 15

- Broad Spectrum SPF 15
  helps protect the skin against
  the sun's harmful rays
- Designed to help moisturize
  the skin
- Designed to help smooth the
  appearance of the skin
- Dermatologist-tested
- Non-comedogenic

1.7 FL OZ/50mL